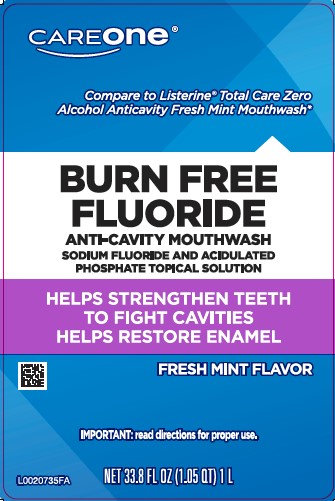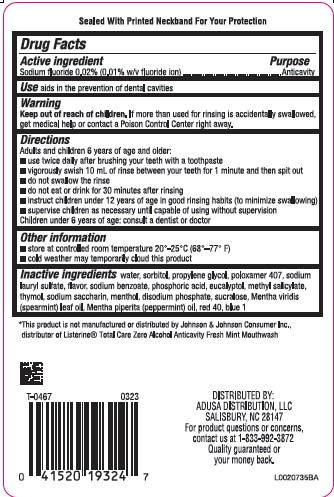 DRUG LABEL: Anticavity
NDC: 72476-971 | Form: RINSE
Manufacturer: Retail Business Services, LLC 
Category: otc | Type: HUMAN OTC DRUG LABEL
Date: 20260206

ACTIVE INGREDIENTS: SODIUM FLUORIDE 0.2 mg/1 mL
INACTIVE INGREDIENTS: WATER; SORBITOL; PROPYLENE GLYCOL; POLOXAMER 407; SODIUM LAURYL SULFATE; SODIUM BENZOATE; PHOSPHORIC ACID; EUCALYPTOL; METHYL SALICYLATE; THYMOL; SACCHARIN SODIUM; MENTHOL; SODIUM PHOSPHATE, DIBASIC, ANHYDROUS; SUCRALOSE; SPEARMINT OIL; PEPPERMINT OIL; FD&C RED NO. 40; FD&C BLUE NO. 1

Care One 971.001/971AB
Burn-Free Fluoride Anti-Cavity Mouthwash

Tamper Evident Statement

Sealed With Printed Neckband for Your Protection

Active ingredient

Sodium fluoride 0.02% (0.01% w/v fluoride ion)

Purpose

Anticavity

Use

aids in the prevention of dental cavities

Warnings

For this product

Keep out of reach of children.

If more than used for rinsing is accidentally swallowed, get medical help or contact a Poison Control Center right away.

Directions

Adults and children 6 years of age and older:

- use twice daily after brushing your teeth with a toothpaste
- vigorously swish 10 mL of rinse between your teeth for 1 minute and then spit out
- do not swallow the rinse
- do not eat or drink for 30 minutes after rinsing
- instruct children under 12 years of age in good rinsing habits (to minimize swallowing)
- supervise children as necessary until capable of using without supervision

Children under 6 years of age: consult a dentist or doctor

Other information

- store at controlled room temperature 20°-25°C (68°–77°F)
- cold weather may temporarily cloud this product

Inactive ingredients

water, sorbitol, propylene glycol, poloxamer 407, sodium lauryl sulfate, flavor, sodium benzoate, phosphoric acid, eucalyptol, methyl salicylate, thymol, sodium saccharin, menthol, disodium phosphate, sucralose, Mentha viridis (spearmint) leaf oil, Mentha piperita (peppermint) oil, red 40, blue 1

Disclaimer

*This product is not manufactured or distributed by Johnson & Johnson Consumer Inc., distributor of Listerine®Total Care Zero Alcohol Anticavity Fresh Mint Mouthwash.

ADVERSE REACTION

DISTRIBUTED BY ADUSA DISTRIBUTION, LLC

SALISBURY, NC 28147

For product questions and concerns, contact us at 1-833-992-3872

Quality guaranteed or your money back.

Principal Panel Display

CAREONE®

Compare to Listerine®Total Care Zero Alcohol Anticavity Fresh Mint Mouthwash*

BURN FREE FLUORIDE

ANTI-CAVITY MOUTHWASH

SODIUM FLUORIDE AND ACIDULATED

PHOSPHATE TOPICAL SOLUTION

HELPS STRENGTHEN TEETH TO FIGHT CAVITIES

HELPS RESTORE ENAMEL

FRESH MINT FLAVOR

IMPORTANT: read directions for proper use.

NET 33.8 FL OZ (1.05 QT) 1 L